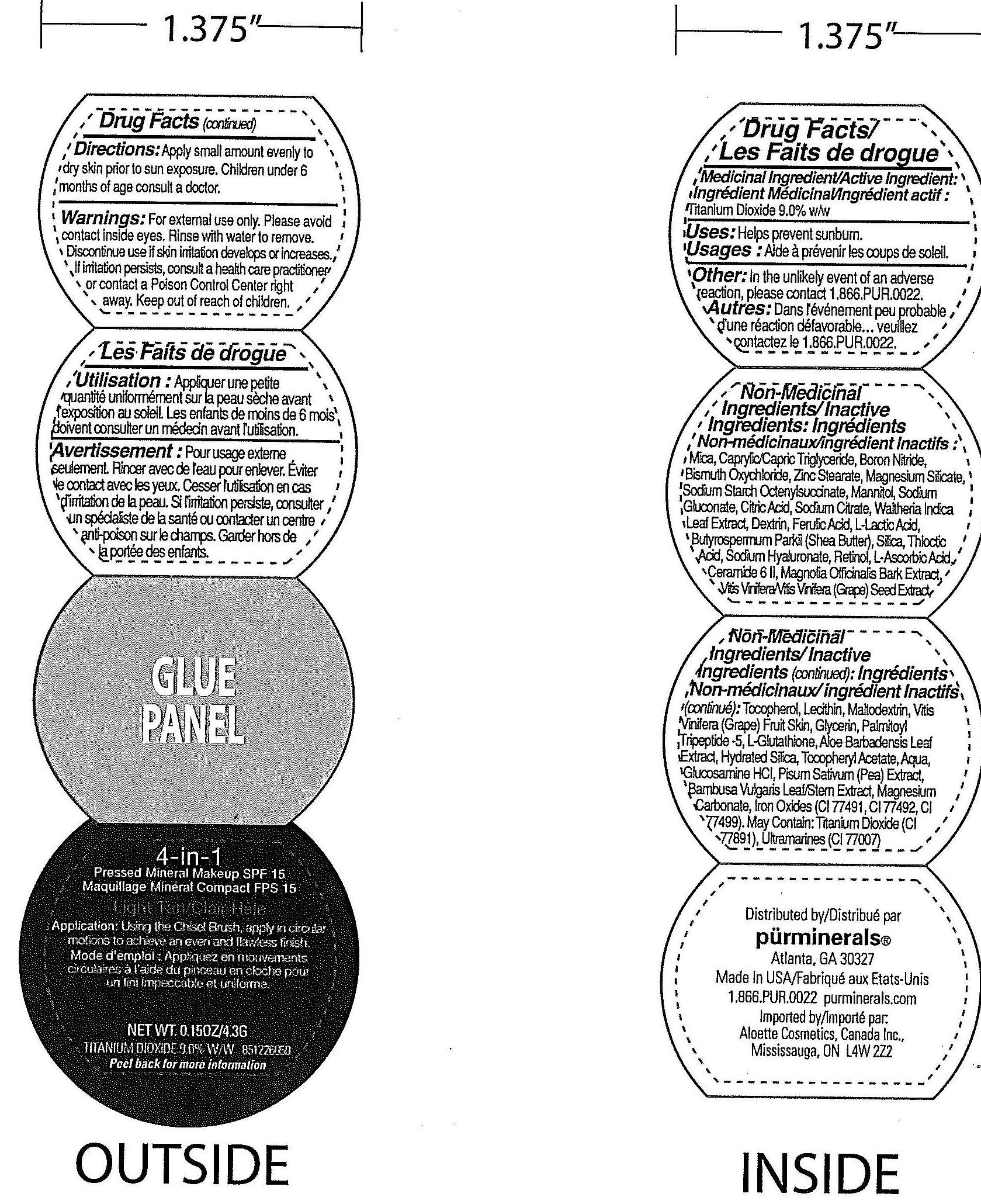 DRUG LABEL: 4 in 1  Pressed Mineral SPF 15 Light
NDC: 67345-6083 | Form: POWDER
Manufacturer: PUR MINERALS
Category: otc | Type: HUMAN OTC DRUG LABEL
Date: 20110915

ACTIVE INGREDIENTS: Titanium Dioxide 0.387 g/4.3 g
INACTIVE INGREDIENTS: Mica; Boron Nitride; MEDIUM-CHAIN TRIGLYCERIDES; Bismuth Oxychloride; Zinc Stearate; Magnesium Silicate; MAGNESIUM CARBONATE; SILICON DIOXIDE; Shea Butter; Acetate Ion; Iron

Active Ingredient : Titanium Dioxide 9 %

Purpose : Sunscreen

STOP USE

Discontinue use If rash or irritation develops and increases. If irritation persists, consult a health care practitioner or Contact a Poison Control Center right away.

Keep Out of Reach of Children .

INACTIVE INGREDIENT

Inactive Ingredients : Mica , Boron Nitride , Caprylic/Capric Triglyceride , Bismuth Oxychloride , Zinc Stearate , Magnesium Silicate , Magnesium Carbonate ,Sodium Starch Octenylsuccinate, Mannitol,

Sodium Gluconate , Citric Acid, Sodium Citrate , Walthena Indica Leaf Extract , Dextrin , Ferulic Acid, L-Lactic Acid, Butyrospermum Parkii (Shea Butter) , Silica, Thioctic Acid,Sodium Hyarluronate, Retinol,

L-Ascorbic Acid, Ceramide 6 II , Magnolia Officinalis Bark Extract, Vitis Vinifera (Grape) Seed Extract , Tocopherol , Lecithin , Maltodextrin , Vitis Vinifera (Grape) Fruit Skin, Glycerin, Palmitoyl Tripeptide-5,

L-Glucothione, Aloe Barbadensis Leaf Extract, Hydrated Silica , Tocopheryl Acetate , Aqua, Glucosamine HCI, Pisum Sativum (Pea) Extract, Bambus Vulgaris Leaf/Stem Extract, Magnesium Carbonate ,

Iron oxide , May contain : Titanium Dioxide, Ultramarines.

WARNINGS

For external use only. Please avoid contact inside eyes. Rinse with water to remove.